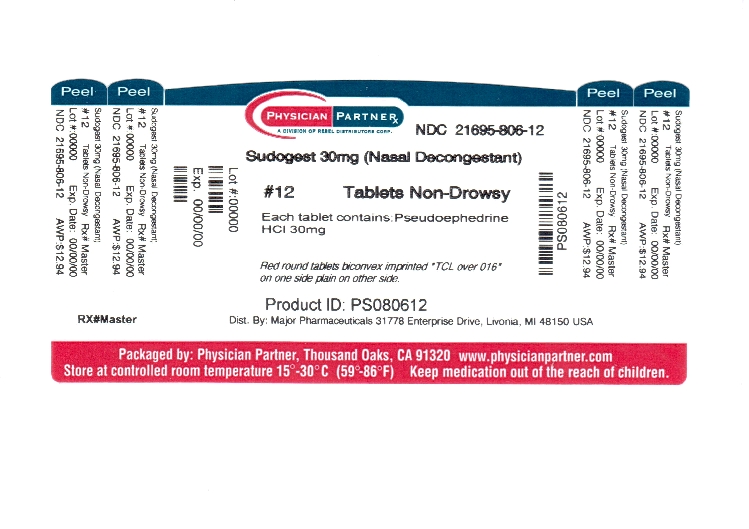 DRUG LABEL: SudoGest
NDC: 21695-806 | Form: TABLET
Manufacturer: Rebel Distributors Corp
Category: otc | Type: HUMAN OTC DRUG LABEL
Date: 20120306

ACTIVE INGREDIENTS: Pseudoephedrine Hydrochloride 30 mg/1 1
INACTIVE INGREDIENTS: Croscarmellose Sodium; FD&C YELLOW NO. 6; HYPROMELLOSES; Magnesium Stearate; Polydextrose; POLYETHYLENE GLYCOLS; Titanium Dioxide; Triacetin

SudoGest
Nasal Decongestant

Active Ingredient (in each tablet)

Pseudoephedrine HCl 30 mg

PURPOSE

Nasal decongestant

USES

- temporarily relieves nasal congestion due to the common cold, hay fever or other upper respiratory allergies, and nasal congestion associated with sinusitis
- temporarily relieves sinus congestion and pressure

WARNINGS

Do not use

if you are now taking a prescription monoamine oxidase inhibitor (MAOI) (certain drugs for depression, psychiatric or emotional conditions, or Parkinson's disease), or for 2 weeks after stopping the MAOI drug. If you do not know if your prescription contains an MAOI, ask a doctor or pharmacist before taking this product.

Ask a doctor before use if you have

- diabetes
- thyroid disease
- heart disease
- high blood pressure
- trouble urinating due to enlargement of the prostate gland

When using this product

- do not exceed recommended dose

Stop use and ask a doctor if

- you get nervous, dizzy or sleepless
- symptoms do not improve within 7 days or occur with fever

If pregrant or breast-feeding,

ask a health professional before use.

Keep out of the reach of children.

In case of overdose, get medical help or contact a Poison Control Center right away

Directions

- take every 4 to 6 hours
- do not exceed 4 doses in 24 hours

adults and children 12 years & over | 2 tablets
children 6 to under 12 years | 1 tablet
children under 6 years | ask a doctor

OTHER INFORMATION

- store at controlled room temperature 15˚-30˚C (59˚-86˚F)
- see end flap for expiration date and lot number

INACTIVE INGREDIENTS

cellulose, croscarmellose sodium, dicalcium phosphate, FD&C red #40, FD&C yellow #6, hypromellose, magnesium stearate, polydextrose, polyethylene glycol, silica gel, titanium dioxide, triacetin